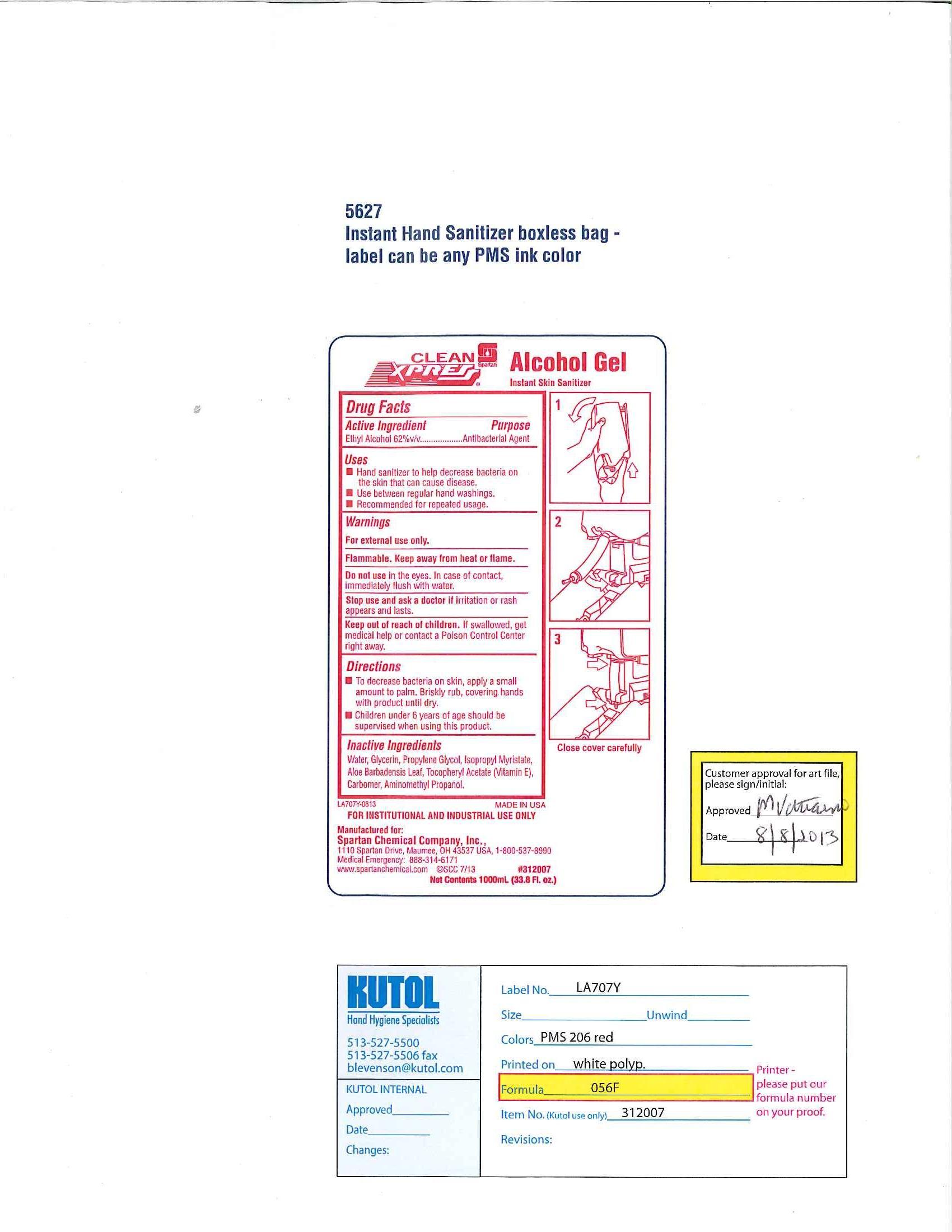 DRUG LABEL: Clean Xpress Alcohol Gel Instant Skin Sanitizer
NDC: 64009-056 | Form: LIQUID
Manufacturer: Spartan Chemical Company, Inc.
Category: otc | Type: HUMAN OTC DRUG LABEL
Date: 20130815

ACTIVE INGREDIENTS: ALCOHOL 65.2 mL/100 mL
INACTIVE INGREDIENTS: ALOE VERA LEAF; WATER; GLYCERIN; PROPYLENE GLYCOL; ISOPROPYL MYRISTATE; AMINOMETHYLPROPANOL; POLYACRYLIC ACID (250000 MW); ALPHA-TOCOPHEROL ACETATE

Clean Xpress Alcohol Gel Instant Skin Sanitizer

ACTIVE INGREDIENT

Ethyl Alcohol 62% v/v

INACTIVE INGREDIENT

Water, Glycerin, Propylene Glycol, Isopropyl Myristate, Aloe Barbadensis Leaf, Tocopheryl Acetate (Vitamin E), Carbomer, Aminomethyl Propanol.

DOSAGE AND ADMINISTRATION

To decrease bacteria on skin, apply a small amount to palm. Briskly rub, covering hands with product until dry.

Children under 6 years of age should be supervised when using this product.

PURPOSE

Hand sanitizer to help decrease bacteria on the skin that can cause disease.

Use between regular handwashings.

Recommended for repeated usage.

INDICATIONS AND USAGE

Hand sanitizer to help decrease bacteria on the skin that can cause disease.

Use between regular hand washings.

Recommended for repeated usage.

Stop use and ask a doctor if irritation or rash appears and lasts. If swallowed get medical help or contact a Posion Control Center right away. Keep out of reach of children.

Keep out of reach of children. If swallowed, get medical help or contact a Poison Control Center right away.

WARNINGS

For external use only.

Flammable. Keep away from heat or flame.

Do not use in the eyes. In case of contact, immediately flush with water.

Stop use and ask a doctor if irritation or rash appears and lasts.

Keep out of reach of children. If swallowed get medical help or contact a Posion Control Center right away.